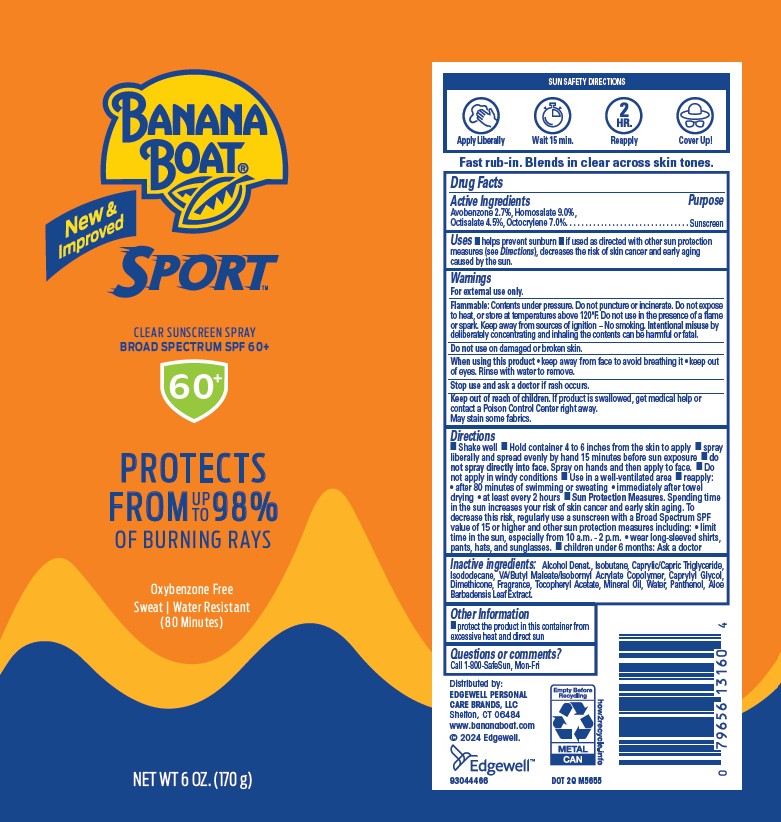 DRUG LABEL: BANANA BOAT
NDC: 63354-471 | Form: SPRAY
Manufacturer: Edgewell Personal Care Brands LLC
Category: otc | Type: HUMAN OTC DRUG LABEL
Date: 20250224

ACTIVE INGREDIENTS: OCTOCRYLENE 7 g/100 g; HOMOSALATE 9 g/100 g; OCTISALATE 4.5 g/100 g; AVOBENZONE 2.7 g/100 g
INACTIVE INGREDIENTS: ALPHA-TOCOPHEROL ACETATE; MINERAL OIL; CAPRYLIC/CAPRIC TRIGLYCERIDE; CAPRYLYL GLYCOL; DIMETHICONE; WATER; PANTHENOL; ISODODECANE; ISOBUTANE; ALCOHOL; ALOE BARBADENSIS LEAF

Active Ingredients

Avobenzone 2.7%, Homosalate 9.0%, Octisalate 4.5%, Octocrylene 7.0%.

Purpose

Sunscreen

Uses

• helps prevent sunburn • if used as directed with other sun protection measures (see Directions), decreases the risk of skin cancer and early aging caused by the sun.

Warnings

For external use only.

Flammable: Contents under pressure. Do not puncture or incinerate. Do not expose to heat, or store at temperatures above 120°F. Do not use in the presence of a flame or spark. Keep away from sources of ignition – No smoking. Intentional misuse by deliberately concentrating and inhaling the contents can be harmful or fatal.

May stain some fabrics.

Do not use

on damaged or broken skin.

When using this product

• keep away from face to avoid breathing it • keep outof eyes. Rinse with water to remove.

Stop use and ask a doctor

if rash occurs.

Keep out of reach of children.

If product is swallowed, get medical help or contact a Poison Control Center right away.

Directions

• Shake well • Hold container 4 to 6 inches from the skin to apply • spray liberally and spread evenly by hand 15 minutes before sun exposure • do not spray directly into face. Spray on hands and then apply to face. • Do not apply in windy conditions • Use in a well-ventilated area • reapply:• after 80 minutes of swimming or sweating • immediately after towel drying • at least every 2 hours • Sun Protection Measures. Spending time in the sun increases your risk of skin cancer and early skin aging. To decrease this risk, regularly use a sunscreen with a Broad Spectrum SPF value of 15 or higher and other sun protection measures including: • limit time in the sun, especially from 10 a.m. - 2 p.m. • wear long-sleeved shirts, pants, hats, and sunglasses. • children under 6 months: Ask a doctor

Inactive ingredients:

Alcohol Denat., Isobutane, Caprylic/Capric Triglyceride, Isododecane, VA/Butyl Maleate/Isobornyl Acrylate Copolymer, Caprylyl Glycol, Dimethicone, Fragrance, Tocopheryl Acetate, Mineral Oil, Water, Panthenol, Aloe Barbadensis Leaf Extract.

Other Information

• protect the product in this container from excessive heat and direct sun

Questions or comments?

Call 1-800-SafeSun, Mon-Fri

Principle Display Panel

BANANA
BOAT
New &
Improved
SPORT
CLEAR SUNSCREEN SPRAY
BROAD SPECTRUM SPF 60+
60+
PROTECTS
FROM UP TO 98%
OF BURNING RAYS
Oxybenzone Free
Sweat | Water Resistant
(80 Minutes)
NET WT 6 OZ (170g)